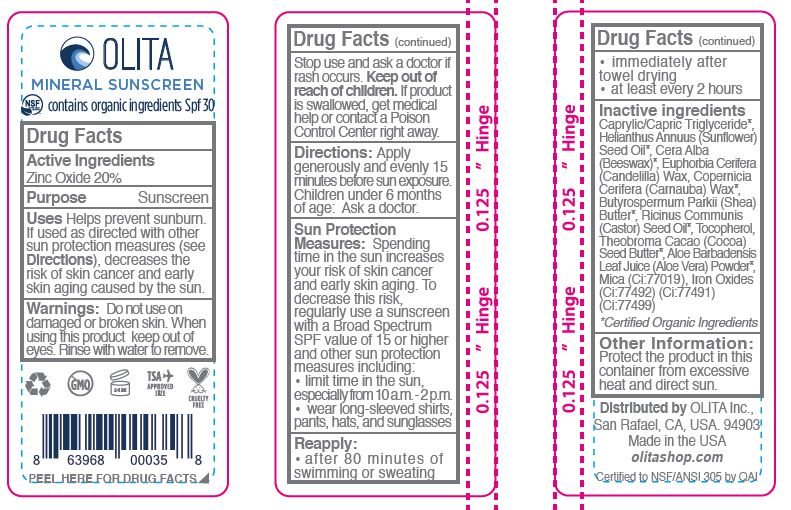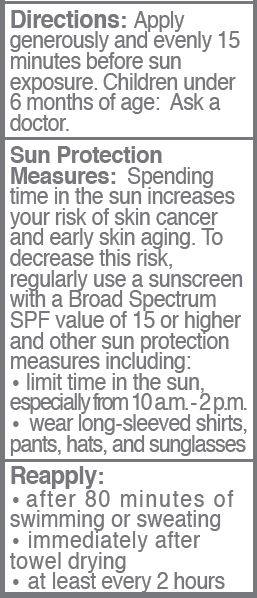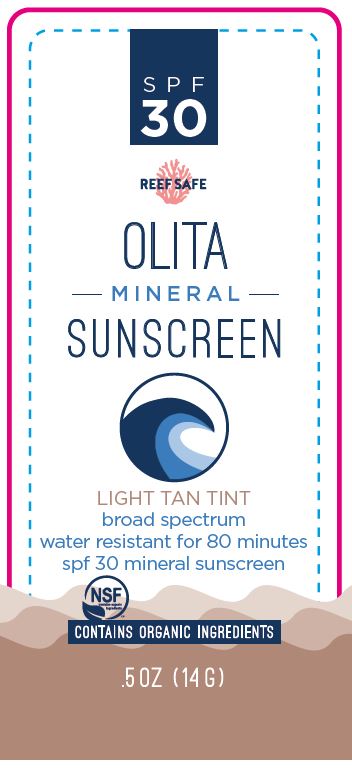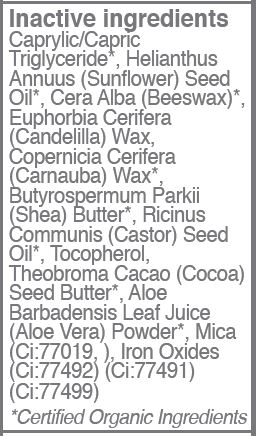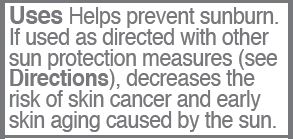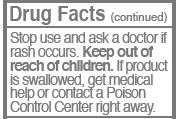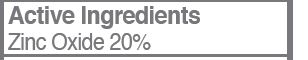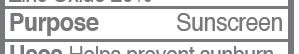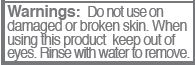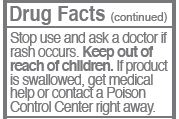 DRUG LABEL: SUNSCREEN
NDC: 62932-214 | Form: STICK
Manufacturer: Private Label Select Ltd CO
Category: otc | Type: HUMAN OTC DRUG LABEL
Date: 20200201

ACTIVE INGREDIENTS: ZINC OXIDE 20 g/100 g
INACTIVE INGREDIENTS: FERRIC OXYHYDROXIDE; SHEA BUTTER; TOCOPHEROL; COCOA BUTTER; MICA; MEDIUM-CHAIN TRIGLYCERIDES; CARNAUBA WAX; FERRIC OXIDE RED; ALOE VERA LEAF; FERROSOFERRIC OXIDE; WHITE WAX; SUNFLOWER OIL; CANDELILLA WAX; CASTOR OIL

Olita Mineral Sunscreen Light Tan Tint, SPF 30